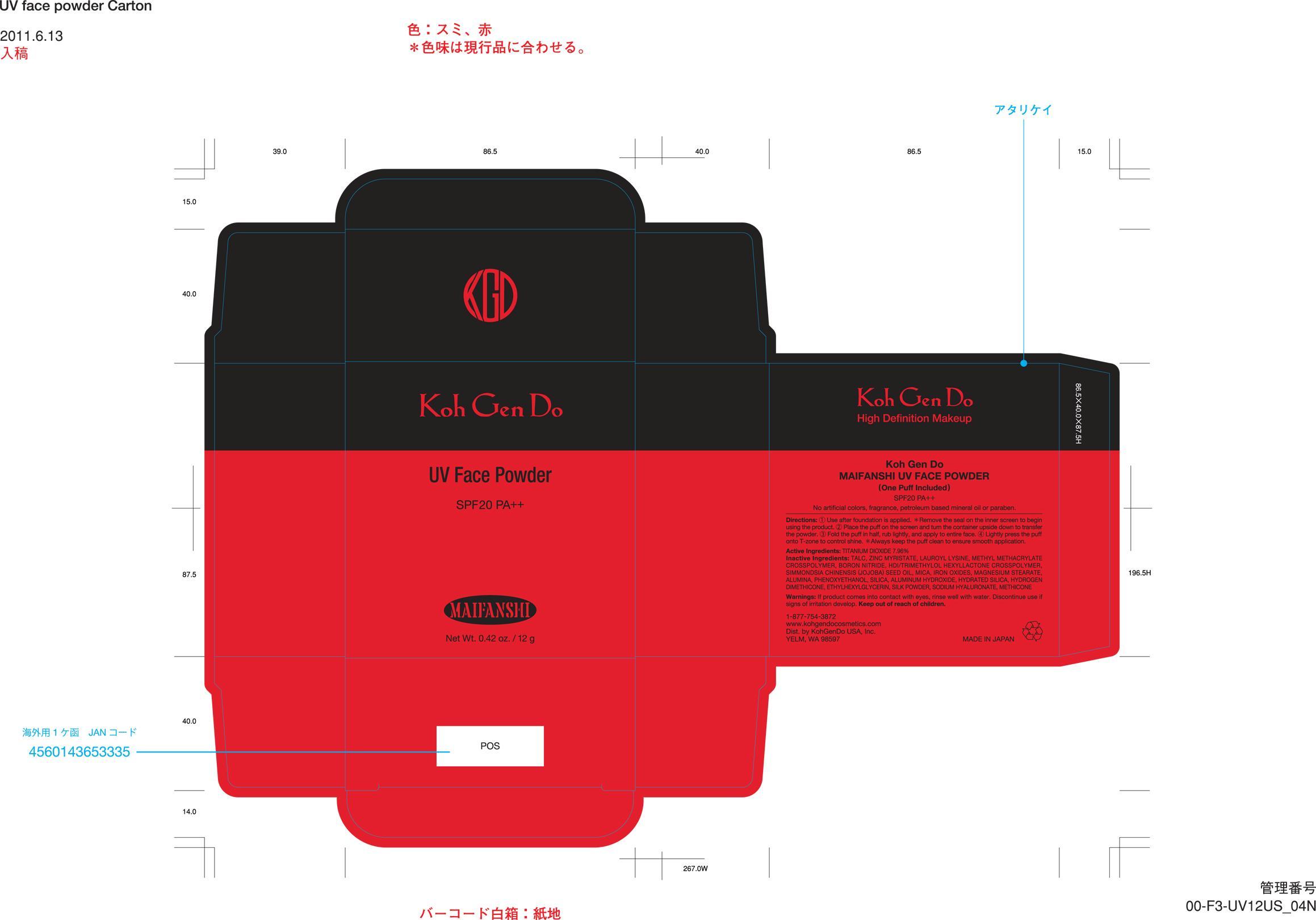 DRUG LABEL: Koh Gen Do Maifanshi UV Face Powder
NDC: 51668-201 | Form: POWDER
Manufacturer: Koh Gen Do USA, Inc
Category: otc | Type: HUMAN OTC DRUG LABEL
Date: 20120711

ACTIVE INGREDIENTS: TITANIUM DIOXIDE 0.9558 g/12 g
INACTIVE INGREDIENTS: TALC; ZINC MYRISTATE; LAUROYL LYSINE; BORON NITRIDE; JOJOBA OIL; MICA; FERRIC OXIDE RED; MAGNESIUM STEARATE; ALUMINUM OXIDE; PHENOXYETHANOL; SILICON DIOXIDE; ALUMINUM HYDROXIDE; HYDRATED SILICA; ETHYLHEXYLGLYCERIN; HYALURONATE SODIUM; METHICONE (20 CST)

Active Ingredients:

TITANIUM DIOXIDE 7.96%

Warnings:

If product comes into contact with eyes, rinse well with water. Discontinue use if signs of irritation develop. Keep out of reach of children.

Directions:

1 Use after foundation is applied. *Remove the seal on the inner screen to begin using the product. 2 Place the puff on the screen and turn the container upside down to transfer the powder. 3 Fold the puff in half, rub lightly, and apply to entire face. 4 Lightly press the puff onto T-zone to control shine. *Always keep the puff clean to ensure smooth application.

DESCRIPTION

(One Puff Included)
SPF20 PA++
No artificial colors, fragrance, petroleum based mineral oil or paraben.

1-877-754-3872

www.kohgendocosmetics.com

Dist. by KohGenDo USA, Inc. YELM, WA 98597

MADE IN JAPAN

Inactive Ingredients:

TALC, ZINC MYRISTATE, LAUROYL LYSINE, BORON NITRIDE, SIMMONDSIA CHINENSIS (JOJOBA) SEED OIL, MICA, IRON OXIDES, MAGNESIUM STEARATE, ALUMINA, PHENOXYETHANOL, SILICA, ALUMINUM HYDROXIDE, HYDRATED SILICA, ETHYHEXYLGLYCERIN, SODIUM HYALURONATE, METHICONE

Principal Display Panel

Koh Gen Do

UV Face Powder

SPF20 PA++

MAIFANSHI

Net Wt. 0.42 oz. / 12 g

Koh Gen Do

High Definition Makeup

Koh Gen Do

MAIFANSHI UV FACE POWDER